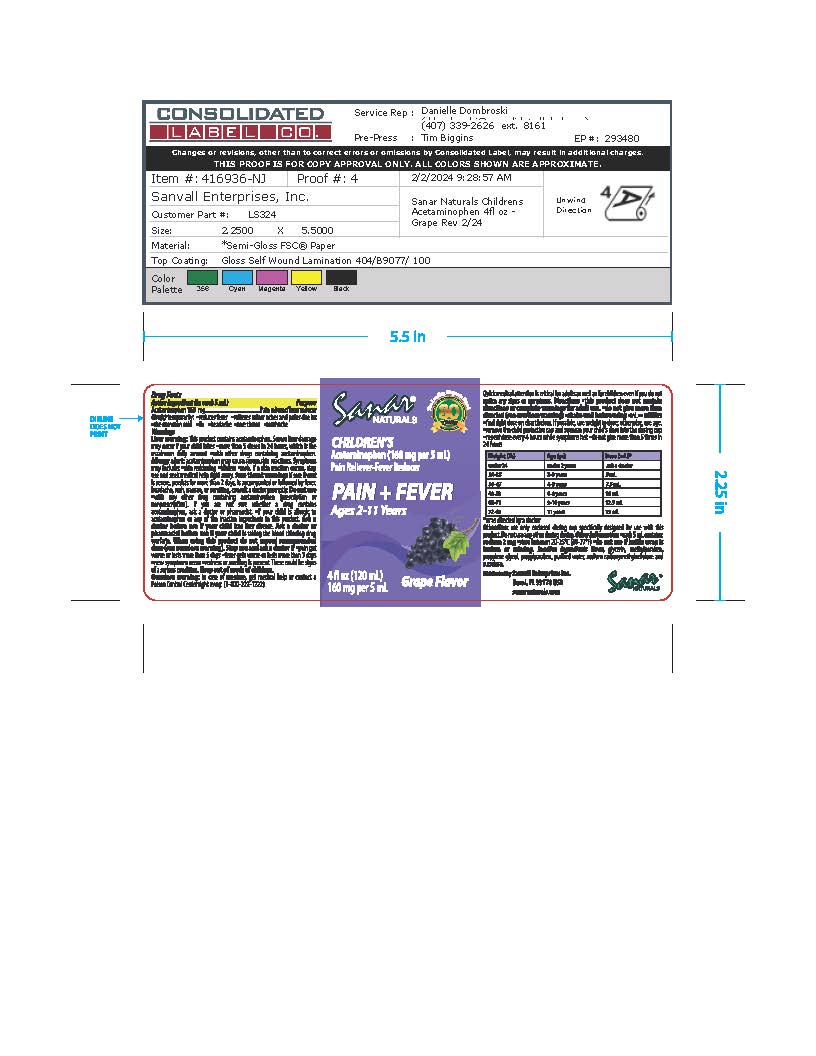 DRUG LABEL: Sanar Naturals Childrens Pain Reliever
NDC: 73386-324 | Form: LIQUID
Manufacturer: Sanvall Enterprises, Inc.
Category: otc | Type: HUMAN OTC DRUG LABEL
Date: 20251002

ACTIVE INGREDIENTS: ACETAMINOPHEN 160 mg/5 mL
INACTIVE INGREDIENTS: PROPYLPARABEN; GLYCERIN; METHYLPARABEN; PROPYLENE GLYCOL; WATER; CARBOXYMETHYLCELLULOSE SODIUM, UNSPECIFIED FORM; SUCRALOSE

Sanar Naturals Childrens Pain Reliever

Active Ingredient

Acetaminophen 160mg

Purpose

Pain reliever/fever reducer

Uses

- reduces fever
- relieves minor aches and pains due to:
- the common cold
- flu
- headache
- sore throat
- toothache

Warnings

Liver warning:This product contains acetaminophen. Severe liver damage may occur if your child takes more than 5 doses in 24 hours, which is the maximum daily amount with other drugs containing acetaminophen.

Allergy alert:Acetaminophen may cause severe skin reactions. Symptoms may include: skin reddening blisters rash. If a skin reaction occurs, stop use and seek medical help right away.

Sore throat warning:if sore throat is severe, persists for more than 2 days, is accompanied or followed by fever, headache, rash, nausea, or vomiting, consult a doctor promptly.

Do not Use

With any other drug containing acetaminophen (prescription or nonprescription). If you are not sure whether a drug contains acetaminophen, ask a doctor or pharmacist. If your child is allergic to acetaminophen or any of the inactive ingredients in this product.

Ask a Doctor

your child has liver disease.

Ask a doctor or pharmacist before use

your child is taking the blood thinning drug warfarin.

When using this product do not exceed recommended dose

Stop use and ask a doctor

if pain gets worse or lasts more than 5 days, fever gets worse or lasts more than 3 days, new symptoms occur, redness or swelling is present. These could be signs of a serious condition.

Keep out of reach of children

in case of overdose, get medical help or contact a Poison Control Center right away. (1-800-222- 1222)

Quick medical attention is critical for adults as well as for children even if you do not notice any signs or symptoms.

Directions

This product does not contain directions or complete warnings for adult use. Do not give more than directed (see overdose warning). Shake well before using. ml=milliliter. Find right dose on chart below. If possible, use weight to dose; otherwise, use age.

Remove the child protective cap and squeeze your child's dose into the dosing cup. Repeat dose every 4 hours while symptoms last, do not give more than 5 times in 24 hours.

Weight (lb) | Age (yr) | Dose (ml)*
under 24 | under 2 years | ask a doctor
24-35 | 2-3 years | 5 ml
36-47 | 4-5 years | 7.5 ml
48-59 | 6-8 years | 10 ml
60-71 | 9-10 years | 12.5 ml
72-95 | 11 years | 15 ml

*or as directed by a doctor

Attention use only enclosed dosing cup specifically designed for use with this product. Do not use any other dosing device.

Inactive Ingredients

Flavor, glycerin, methylparaben, propylene glycol, propylparaben, purified water, sodium carboxymethylcellulose and sucralose.

Other Information

www.sanarnaturals.com